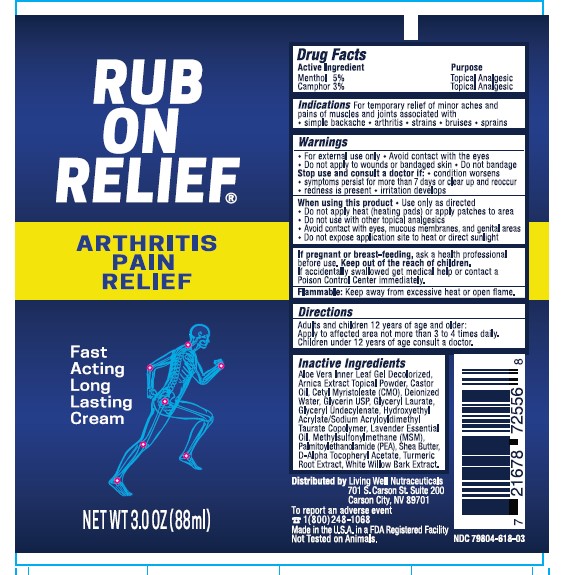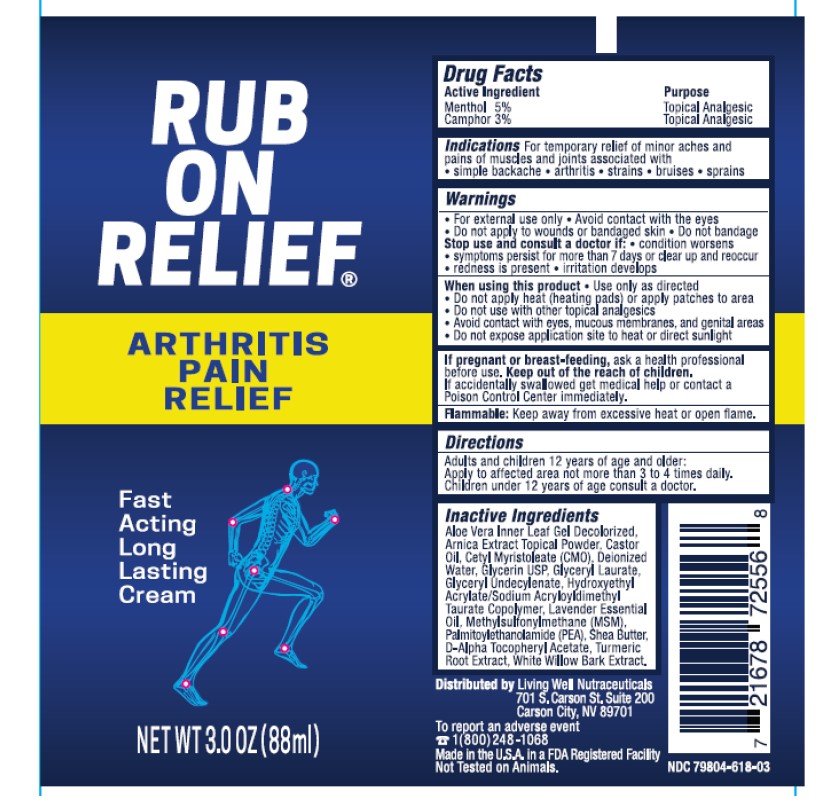 DRUG LABEL: Healthy Back Institute Rub On Relief
NDC: 83084-618 | Form: CREAM
Manufacturer: Fullstack Fulfillment
Category: otc | Type: HUMAN OTC DRUG LABEL
Date: 20260126

ACTIVE INGREDIENTS: CAMPHOR (SYNTHETIC) 0.03 g/1 g; MENTHOL 0.05 g/1 g
INACTIVE INGREDIENTS: CASTOR OIL; LAVENDER OIL; 1-PALMITOYL-2-OLEOYL-SN-GLYCERO-3-(PHOSPHO-RAC-(1-GLYCEROL)); WILLOW BARK; ARNICA MONTANA FLOWER; DISODIUM .ALPHA.-TOCOPHERYL PHOSPHATE, D-; CETYL MYRISTOLEATE; GLYCERYL LAURATE; GLYCERYL RICINOLEATE; DEMETON-S-METHYLSULFONE; ALOE VERA LEAF; GLYCERIN; HYDROXYETHYL ACRYLATE/SODIUM ACRYLOYLDIMETHYL TAURATE COPOLYMER (45000 MPA.S AT 1%); SHEA BUTTER; TURMERIC; WATER

Purpose

Topical Analgesic

Indications

For temporary relief of minor aches andf Pains of muscles joints.

Warning

For external use only

When Using

Use only as directed.

Stop Use

Stop use and consult a doctor if conditions worsens.

Pregnancy or Breast feeding

Ask a health professional before use.

PACKAGE LABEL

ACTIVE INGREDIENT

Menthol 5%

Camphor 3%